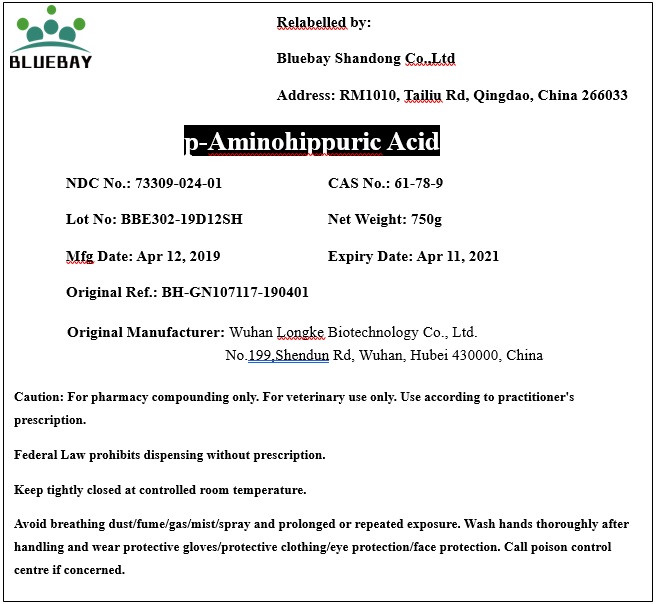 DRUG LABEL: p-Aminohippuric Acid
NDC: 73309-024 | Form: POWDER
Manufacturer: BLUEBAY SHANDONG CO.,LTD
Category: other | Type: BULK INGREDIENT
Date: 20190906

ACTIVE INGREDIENTS: AMINOHIPPURIC ACID 1 g/1 g

p-Aminohippuric Acid